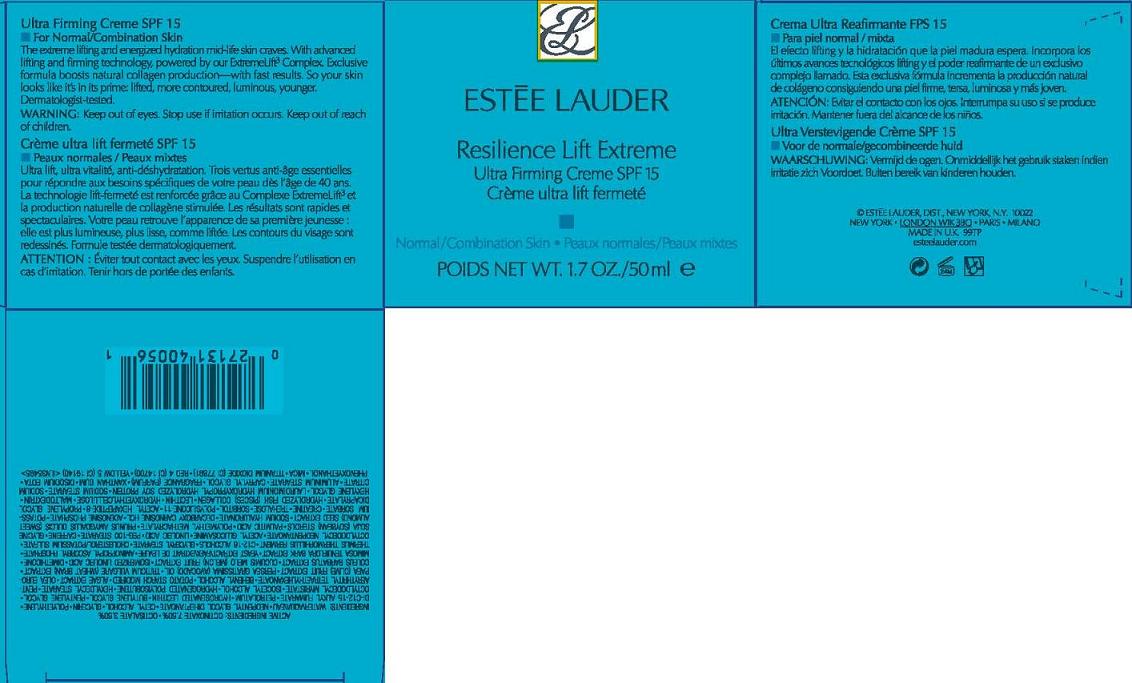 DRUG LABEL: RESILIENCE LIFT
NDC: 11559-932 | Form: CREAM
Manufacturer: ESTEE LAUDER INC
Category: otc | Type: HUMAN OTC DRUG LABEL
Date: 20110621

ACTIVE INGREDIENTS: OCTINOXATE 7.5 mL/100 mL; OCTISALATE 3.5 mL/100 mL
INACTIVE INGREDIENTS: WATER; NEOPENTYL GLYCOL DIHEPTANOATE; CETYL ALCOHOL; GLYCERIN; PETROLATUM; HYDROGENATED SOYBEAN LECITHIN; BUTYLENE GLYCOL; PENTYLENE GLYCOL; OCTYLDODECYL MYRISTATE; ISOCETYL ALCOHOL; DOCOSANOL; STARCH, POTATO; OLIVE OIL; AVOCADO OIL; WHEAT BRAN; PLECTRANTHUS BARBATUS ROOT; CUCUMBER; DIMETHICONE; ALBIZIA JULIBRISSIN BARK; YEAST; C12-16 ALCOHOLS; GLYCERYL MONOSTEARATE; CHOLESTEROL; POTASSIUM SULFATE; OCTYLDODECYL NEOPENTANOATE; LINOLEIC ACID; PEG-100 STEARATE; CAFFEINE; SOY STEROL; PALMITIC ACID; ALMOND OIL; HYALURONATE SODIUM; ADENOSINE PHOSPHATE; POTASSIUM SORBATE; CREATINE; TREHALOSE; SORBITOL; ACETYL HEXAPEPTIDE-3; PROPYLENE GLYCOL DICAPRYLATE; LECITHIN, SOYBEAN; MALTODEXTRIN; HEXYLENE GLYCOL; SODIUM CITRATE; CAPRYLYL GLYCOL; EDETATE DISODIUM; PHENOXYETHANOL; MICA; TITANIUM DIOXIDE; FD&C RED NO. 4; FD&C YELLOW NO. 5

ACTIVE INGREDIENTS: OCTINOXATE 7.50% [] OCTISALATE 3.50%

INACTIVE INGREDIENT

INACTIVE INGREDIENTS: WATER [] NEOPENTYL GLYCOL DIHEPTANOATE [] CETYL ALCOHOL [] GLYCERIN [] POLYETHYLENE [] DI-C12-15 ALKYL FUMARATE [] PETROLATUM [] HYDROGENATED LECITHIN [] BUTYLENE GLYCOL [] PENTYLENE GLYCOL [] OCTYLDODECYL MYRISTATE [] ISOCETYL ALCOHOL [] HYDROGENATED POLYISOBUTENE [] HEXYLDECYL STEARATE [] PENTAERYTHRITYL TETRAETHYLHEXANOATE [] BEHENYL ALCOHOL [] POTATO STARCH MODIFIED [] ALGAE EXTRACT [] OLEA EUROPAEA (OLIVE) FRUIT EXTRACT [] PERSEA GRATISSIMA (AVOCADO) OIL [] TRITICUM VULGARE (WHEAT BRAN) EXTRACT [] COLEUS BARBATUS EXTRACT [] CUCUMIS MELO (MELON) FRUIT EXTRACT [] ISOMERIZED LINOLEIC ACID [] DIMETHICONE [] MIMOSA TENUIFLORA BARK EXTRACT [] YEAST EXTRACT\FAEX\EXTRAIT DE LEVURE [] AMINOPROPYL ASCORBYL PHOSPHATE [] THERMUS THERMOPHILLUS FERMENT [] C12-16 ALCOHOLS [] GLYCERYL STEARATE [] CHOLESTEROL/POTASSIUM SULFATE [] OCTYLDODECYL NEOPENTANOATE [] ACETYL GLUCOSAMINE [] LINOLEIC ACID [] PEG-100 STEARATE [] CAFFEINE [] GLYCINE SOJA (SOYBEAN) STEROLS [] PALMITIC ACID [] POLYMETHYL METHACRYLATE [] PRUNUS AMYGDALUS DULCIS (SWEET ALMOND) SEED EXTRACT [] SODIUM HYALURONATE [] DECARBOXY CARNOSINE HCL [] ADENOSINE PHOSPHATE [] POTASSIUM SORBATE [] CREATINE [] TREHALOSE [] SORBITOL [] POLYSILICONE-11 [] ACETYL HEXAPEPTIDE-8 [] PROPYLENE GLYCOL DICAPRYLATE [] HYDROLYZED FISH (PISCES) COLLAGEN [] LECITHIN [] HYDROXYETHYLCELLULOSE [] MALTODEXTRIN [] HEXYLENE GLYCOL [] LAURDIMONIUM HYDROXYPROPYL HYDROLYZED SOY PROTEIN [] SODIUM STEARATE [] SODIUM CITRATE [] ALUMINUM STEARATE [] CAPRYLYL GLYCOL [] FRAGRANCE (PARFUM) [] XANTHAN GUM [] DISODIUM EDTA [] PHENOXYETHANOL [] MICA [] TITANIUM DIOXIDE (CI 77891) [] RED 4 (CI 14700) [] YELLOW 5 (CI 19140)

WARNINGS

WARNING: KEEP OUT OF EYES. STOP USE IF IRRITATION OCCURS. KEEP OUT OF REACH OF CHILDREN.

PACKAGE LABEL

PRINCIPAL DISPLAY PANEL:

ESTEE LAUDER

RESILIENCE LIFT EXTREME

ULTRA FIRMING CREME

SPF 15

NORMAL/COMBINATION SKIN

NT WT. 1.7 OZ./50 ML

ESTEE LAUDER INC DIST

NEW YORK, NY 10022